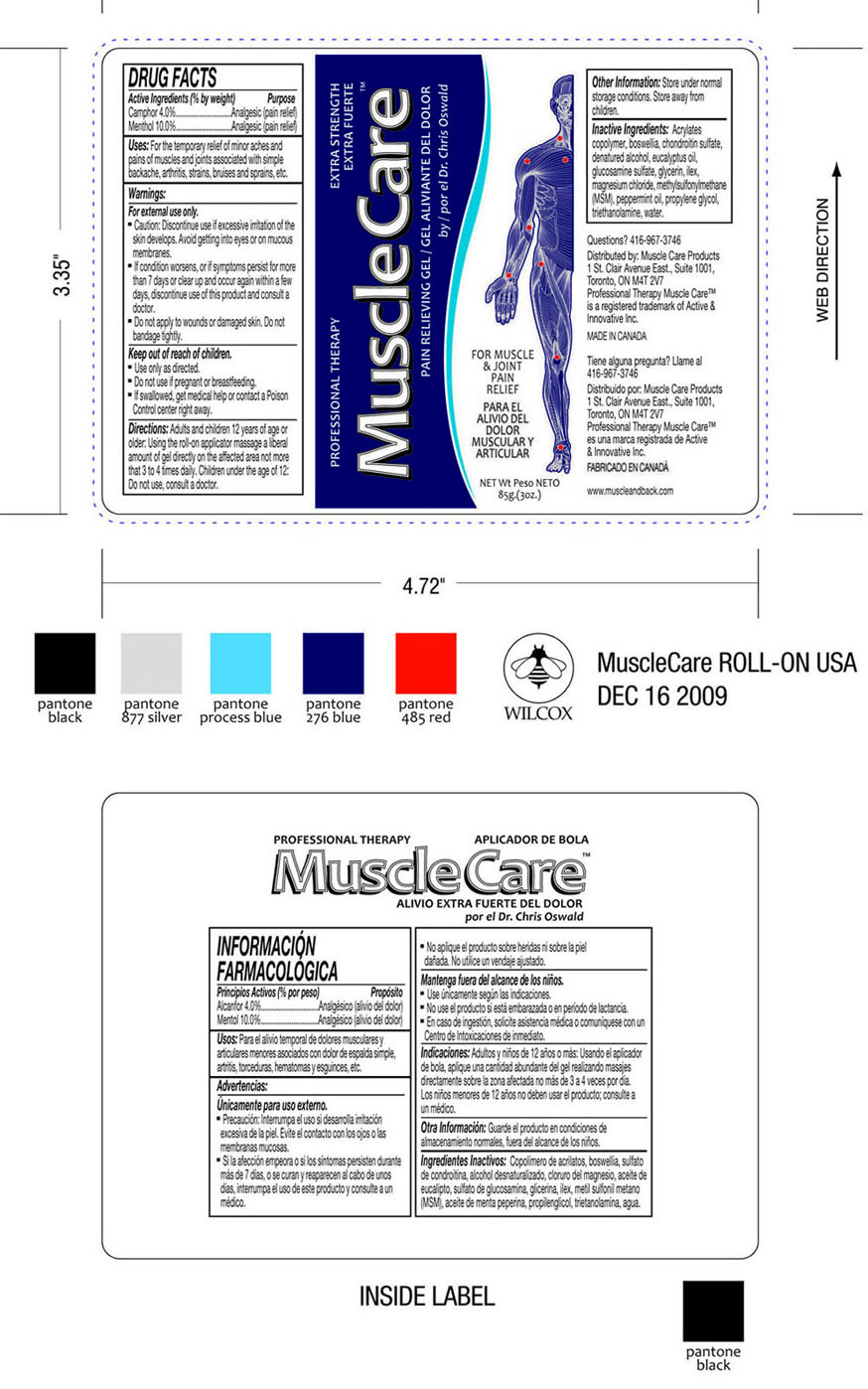 DRUG LABEL: Camphor, Menthol
NDC: 50421-002 | Form: GEL
Manufacturer: Active & Innovative Inc.
Category: otc | Type: HUMAN OTC DRUG LABEL
Date: 20100113

ACTIVE INGREDIENTS: CAMPHOR 3.4 g/85 g; MENTHOL 8.5 g/85 g
INACTIVE INGREDIENTS: EUCALYPTUS OIL; GLUCOSAMINE SULFATE; GLYCERIN; MAGNESIUM CHLORIDE; DIMETHYL SULFONE; PEPPERMINT OIL; PROPYLENE GLYCOL; TROLAMINE; WATER

DRUG FACTS

Active Ingredients (% by weight)

Camphor 4.0%

Menthol 10.0%

Purpose

Analgesic (pain relief)

Uses

For the temporary relief of minor aches and pains of muscles and joints associated with simple backache, arthritis, strains, bruises and sprains, etc.

Warnings

- For external use only.
- Caution: Discontinue use if excessive irritation of the skin develops. Avoid getting into eyes or on mucous membranes.
- If the conditions worsens, or if the symptoms persists for more than 7 days or clears up and occurs again within a few days, discontinue use of this product and consult a doctor.
- Do not apply to wounds or damaged skin. Do not bandage tightly.

OTC - Keep Out of Reach of Children Section

Keep out of reach of children.

Other Warnings

- Use only as directed.
- Do not use if pregnant or breastfeeding.
- If swallowed, get medical help or contact a poison Control center right away.

Directions

Adults and children12 years of age or older: Using the roll on applicator massage a liberal amount of gel directly on the affected area not more than 3 or 4 times daily.
Children under the age of 12: Do not use, consult a doctor.

Other Information

Store under normal storage conditions. Store away from Children.

Inactive Ingredients

Acrylates copolymer, boswellia, chondroitin sulphate, denatured alcohol, eucalyptus oil, glucosamine sulphate, glycerin,ilex, magnesium chloride, methylsulfonylmethane (MSM), peppermint oil, propylene glycol,triethanolamine, water.

Questions?

416-967-3746

Principal Display Panel

PROFESSIONAL THERAPY EXTRA STRENGTH
EXTRA FUERTE
MuscleCare TM
PAIN RELIEVING GEL/ GEL ALIVIANTE DEL DOLOR
by/ por el Dr. Chris Oswald
FOR MUSCLE
& JOINT
PAIN
RELIEF
PARA EL
ALIVIO DEL
DOLOR
MUSCULAR Y
ARTICULAR
NET Wt. Peso. NETO
85g (3OZ.)
Distributed by: Muscle care products
1st. Clair Avenue East, Suite 1001,
Toronto, ON M4T 2V7
Professional Therapy Muscle Care TM
is a registered trademark of Active &
Innovative Inc.
MADE IN CANADA.
Tiene alguna pregunta? Llame al
415-967-3746
Distribuido por: Muscle care products
1st. Clair Avenue East, Suite 1001,
Toronto, ON M4T 2V7
Professional Therapy Muscle Care TM
es una marca registrada de Active &
Innovative Inc.
FABRICADO EN CANADA
www.muscleandback.com